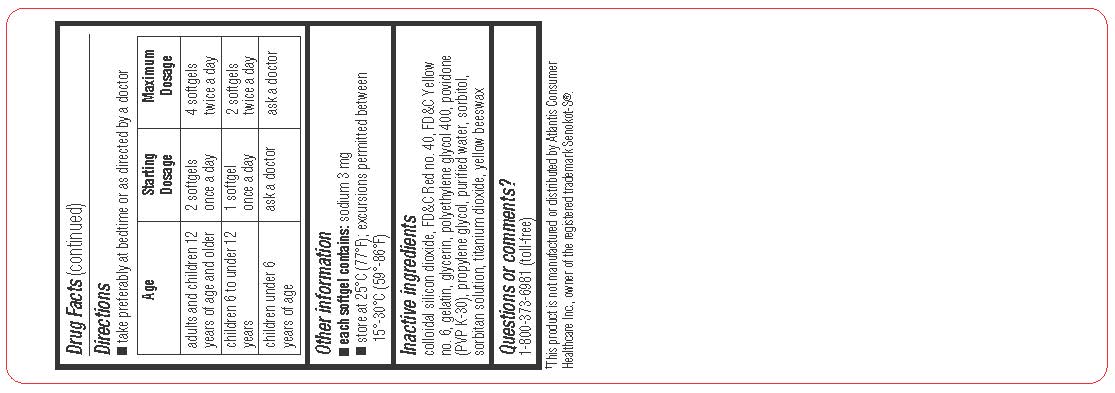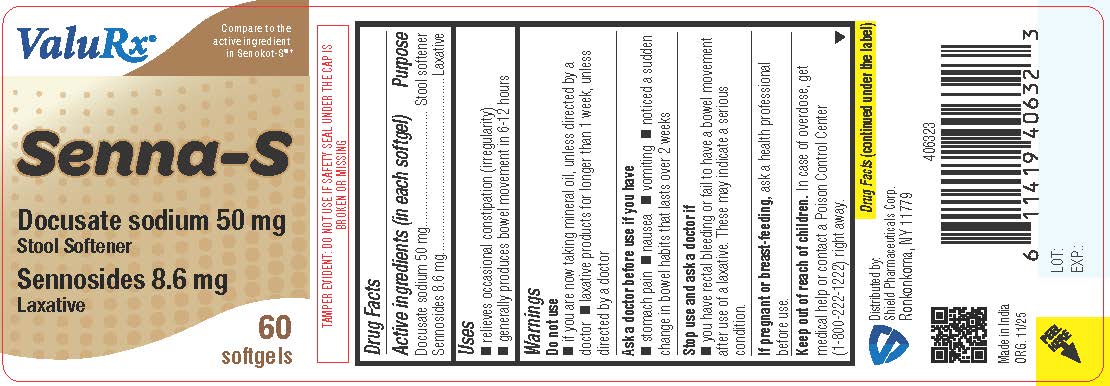 DRUG LABEL: Senna S
NDC: 83059-0120 | Form: CAPSULE, LIQUID FILLED
Manufacturer: Shield Pharmaceuticals Corp
Category: otc | Type: HUMAN OTC DRUG LABEL
Date: 20251205

ACTIVE INGREDIENTS: DOCUSATE SODIUM 50 mg/1 1; SENNOSIDES 8.6 mg/1 1
INACTIVE INGREDIENTS: POLYETHYLENE GLYCOL 400; PROPYLENE GLYCOL; POVIDONE; FD&C YELLOW NO. 6; FD&C RED NO. 40; SILICON DIOXIDE; GELATIN; GLYCERIN; SORBITOL; SORBITAN; WATER; SYNTHETIC BEESWAX; TITANIUM DIOXIDE

Senna S

Active ingredients (in each tablet)

Docusate sodium 50 mg
Sennosides 8.6 mg

Purpose

Stool softener

Laxative

Uses

- relieves occasional constipation (irregularity)
- generally produces bowel movement in 6-12 hours

Warnings

Do not use

- if you are now taking mineral oil, unless directed by a doctor
- laxative products for longer than 1 week unless directed by a doctor

Ask a doctor before use if you have

- stomach pain
- nausea
- vomiting
- noticed a sudden change in bowel habits that continues over a periodof 2 weeks

Stop use and ask a doctor if

you have rectal bleeding or fail to have a bowel movement after use of a laxative. These may indicate a serious condition.

If pregnant or breast-feeding,

ask a health professional before use.

Keep out of reach of children.

In case of overdose, get medical help or contact a Poison Control Center (1-800-222-1222) right away.

Directions

- take preferably at bedtime or as directed by a doctor

age | starting dosage | maximum dosage
adults and children 12 years of age or older | 2 softgels once a day | 4 softgels twice a day
children 6 to under 12 years | 1 softgel once a day | 2 softgels twice a day
children under 6 years of age | ask a doctor | ask a doctor

Other information

- each softgel contains: calcium 3 mg
- store at 25ºC (77ºF); excursions permitted between 15-30ºC (59-86ºF)

Inactive ingredients

Colloidal Silicon Dioxide, FD&C Red 40, FD&C yellow No. 6, Gelatin, Glycerin, Polyethylene Glycol -400, Propylene Glycol, Povidone (PVPK-30), Purified Water, Sorbitol Sorbitan Solution, Titanium Dioxide, yellow bees wax

Questions or comments?

Call 1-800-373-6981 Monday-Friday 9AM-5PM EST

Distributed by:
Shield Pharmaceuticals LLCRonkonkoma, NY 11779

PACKAGE LABEL

Senna-S

Docusate Sodium 50 mg and
Sennosides 8.6 mg

Label